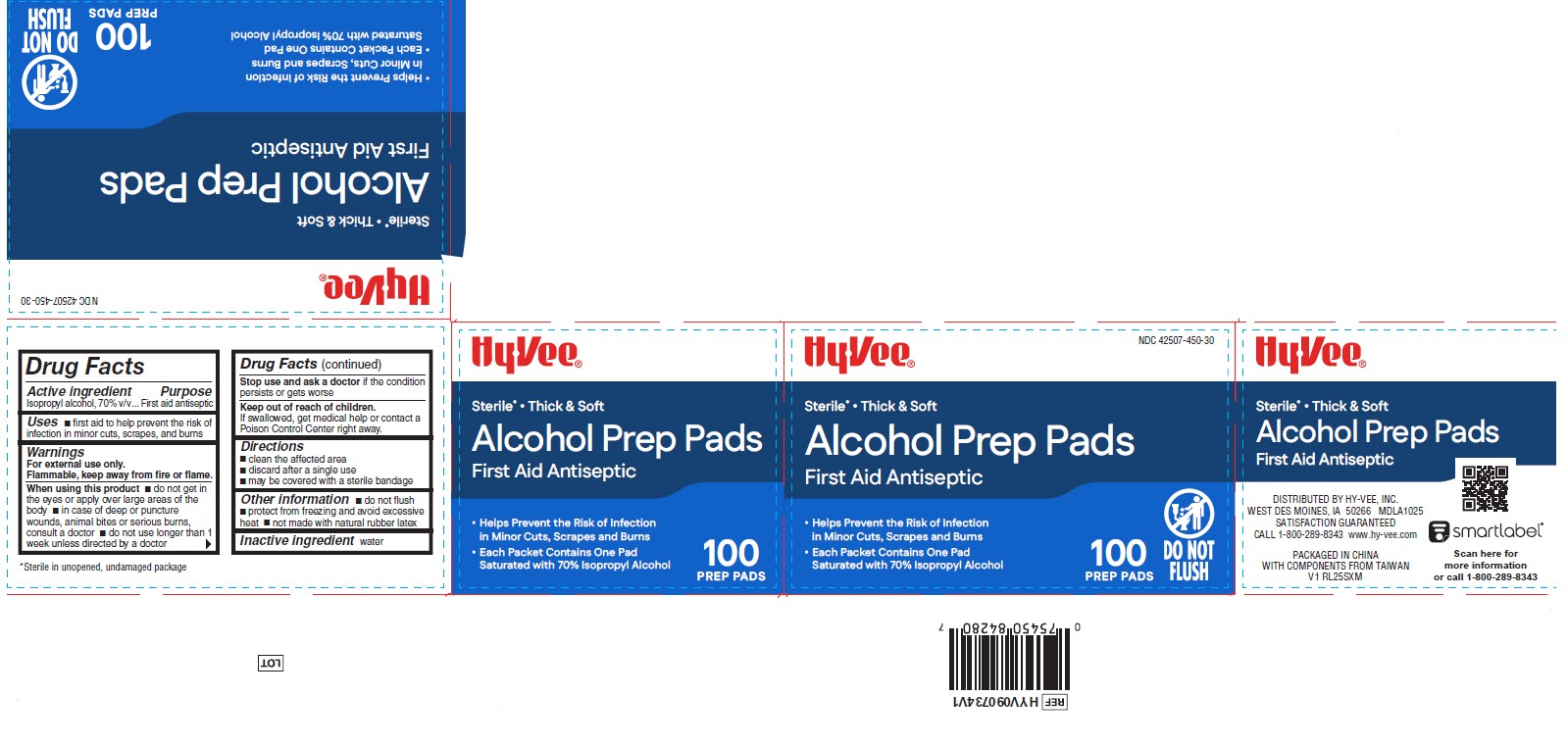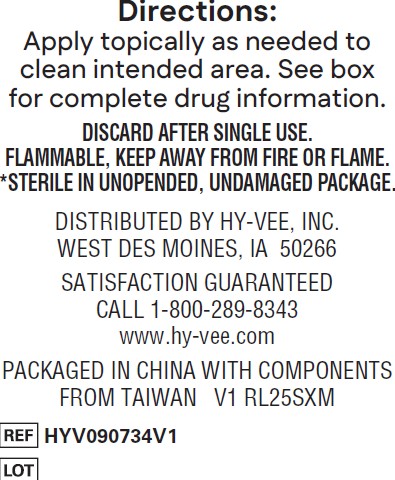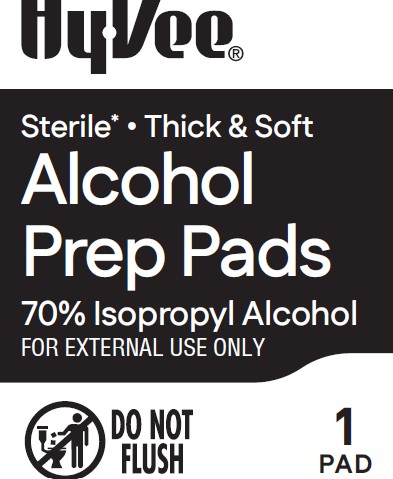 DRUG LABEL: Medline
NDC: 42507-450 | Form: SWAB
Manufacturer: Hy-Vee, Inc.
Category: otc | Type: HUMAN OTC DRUG LABEL
Date: 20260210

ACTIVE INGREDIENTS: ISOPROPYL ALCOHOL 70 mL/100 mL
INACTIVE INGREDIENTS: WATER

42507-450 Hyvee IPA Prep Pads

Active Ingredient

Isopropyl acohol, 70% v/v

Purpose

First aid antiseptic

Uses

- first aid to help prevent the risk of infection in minor cuts, scrapes, and burns

Warnings

For external use only.

Flammable, keep away from fire or flame.

When using this product

- do not get into eyes or apply over large areas of the body
- in case of deep or puncture wounds, animal bites or serious burns, consult a doctor
- do not use longer than 1 week unless directed by a doctor

Stop use and ask a doctor

if the condition persists or gets worse

Keep out of reach of children

If swallowed, get medical help or contact a Poison Control Center right away.

Directions

- clean the affected area
- discard after a single use
- may be covered with a sterile bandage

Other information

- do not flush
- protect from freezing and avoid excessive heat
- not made with natural rubber latex

Inactive ingredient

water

Manufacturer Information

DISTRIBUTED BY HY-VEE, INC.

WEST DES MOINES, IA 50266 MDLA1025

SATISFACTION GUARANTEED

CALL 1-800-289-8343 www.hy-vee.com

PACKAGED IN CHINA

WITH COMPONENTS FROM TAIWAN